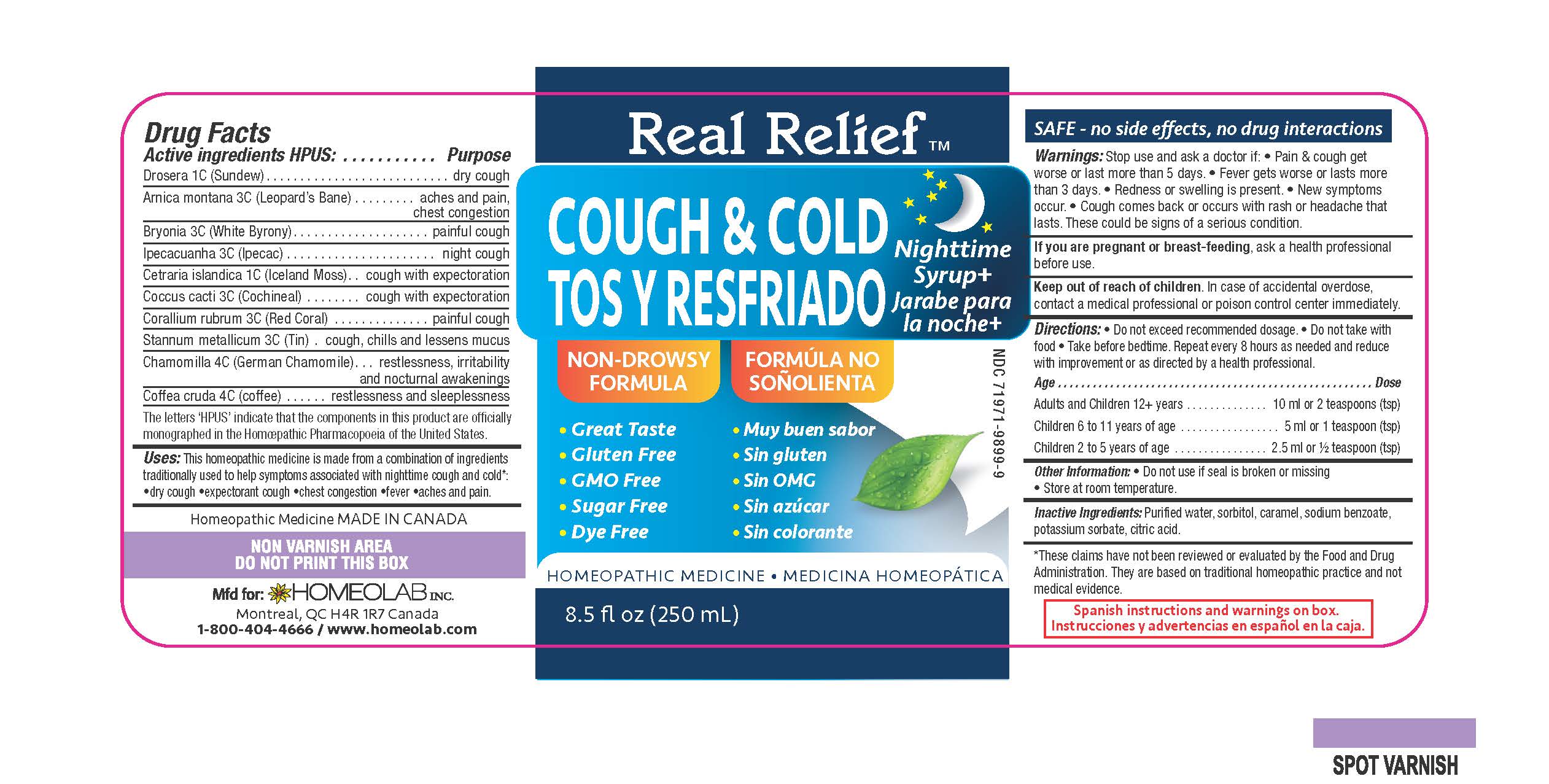 DRUG LABEL: Real Relief
NDC: 63388-989 | Form: LIQUID
Manufacturer: Laboratoire Atlas Inc
Category: homeopathic | Type: HUMAN OTC DRUG LABEL
Date: 20251008

ACTIVE INGREDIENTS: DROSERA ROTUNDIFOLIA FLOWERING TOP 1 [hp_C]/100 mL; ARNICA MONTANA 3 [hp_C]/100 mL; BRYONIA ALBA WHOLE 3 [hp_C]/100 mL; IPECAC 3 [hp_C]/100 mL; CETRARIA ISLANDICA SUBSP. ISLANDICA 1 [hp_C]/100 mL; PROTORTONIA CACTI 3 [hp_C]/100 mL; CORALLIUM RUBRUM WHOLE 3 [hp_C]/100 mL; TIN 3 [hp_C]/100 mL; CHAMOMILE 4 [hp_C]/100 mL; ARABICA COFFEE BEAN 4 [hp_C]/100 mL
INACTIVE INGREDIENTS: WATER; SORBITOL; CARAMEL; SODIUM BENZOATE; POTASSIUM SORBATE; CITRIC ACID MONOHYDRATE

Active Ingredients HPUS:

Drosera 1C (Sundew)

Arnica montana 3C (Leopards Bane)

Bryonia 3C (Whte Bryony)

Ipecacuanha 3C (Ipecac)

Cetraria islandica 1C (Iceland Moss)

Coccus cacti 3C (Cochineal)

Corallium rubrum 3C (Red Coral)

Stannum metallicum 3C (Tin)

Camomilla 4C (German Chamomille)

Coffea crudea 4C (coffee)

Purpose

Drosera 1C......................................dry cough

Arnica montana 3C...........................aches and pains, chest congestion

Bryonia 3C......................................painful cough

Ipecacuanha 3C...............................night cough

Cetraria islandica 1C.........................cough with expectoration

Coccus cacti 3C................................cough with expectoration

Corallium rubrum 3C.........................painful cough

Stannum metallicum 3C.....................cough, chills, and lessens mucus

Camomilla 4C...................................restlessness, irritability, nocturnal awakenings

Coffea crudea 4C..............................restlessness and sleeplessness

The letters "HPUS" indicate that the components in this product are officially

monographed in the Homeopathic Pharcopoeia of the United States

INDICATIONS AND USAGE

Uses This homeopathic medicine is made from a combination

of ingredients traditionally used to help relieve

symptoms associated with nighttime cough and cold*:

•dry cough •cough with expectoration

•chest congestion •fever •aches and pains

Warnings

Stop use and ask a doctor if •Pain & cough gets worse

or lasts more than 5 days

•Fever gets worse or lasts more than 3 days •Redness

or swelling is present •New symptoms occur •Cough

comes back or occurs with rash or headache that lasts.

These could be signs of a serious condition

If you are pregnant or breastfeeding, ask a health professional before use.

Keep out of reach of children.In case of accidental

overdose, contact a medical professional or a poison

control center immediately.

DOSAGE AND ADMINISTRATION

Directions •Do not exceed recommended dosage •Do not take with

food •Take before bedtime. Repeat every 8 hours as needed and reduce

with improvement or as directed by a health care professional.

Age..................................................................... Dose

Adults and Children 12 + years...............................10 ml or 2 teaspoons (tsp)

Children 6 to 11 years of age..................................5 ml or 1 teaspoon (tsp)

Children 2 to 5 years of age....................................2.5 ml or 1/2 teaspoon (tsp)

Other information •do not use if seal is broken or missing

•Store at room temperature.

Inactive ingredients Purified water, sorbitol,

caramel, sodium benzoate, potassium sorbate, citric acid